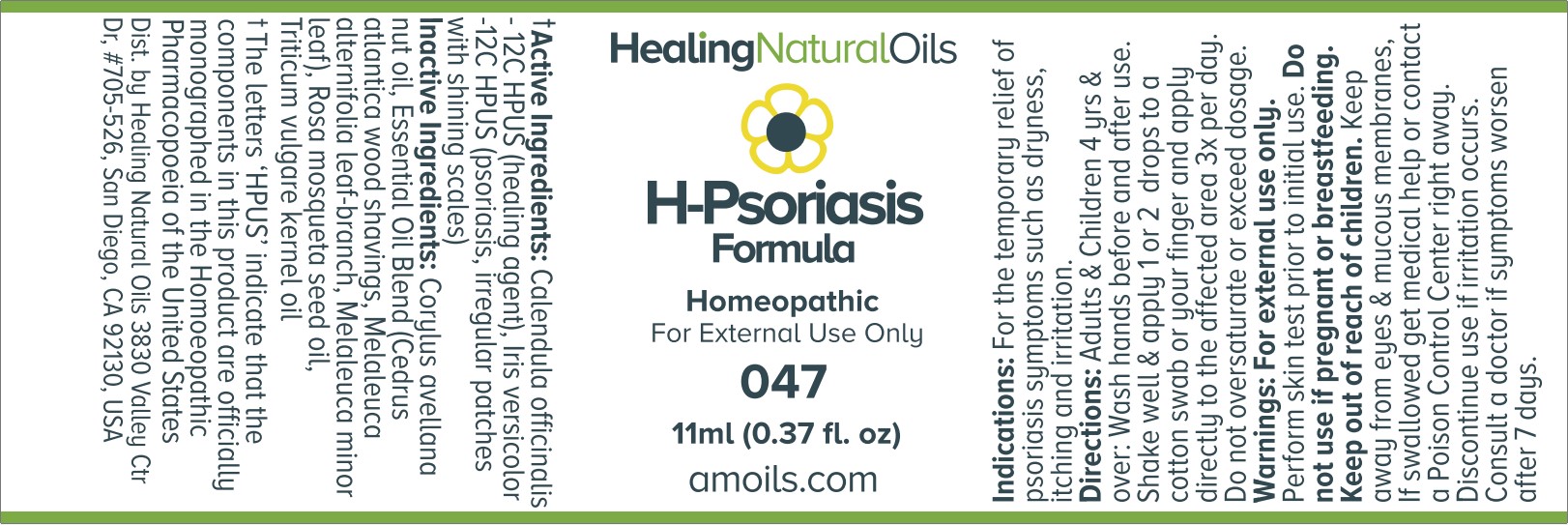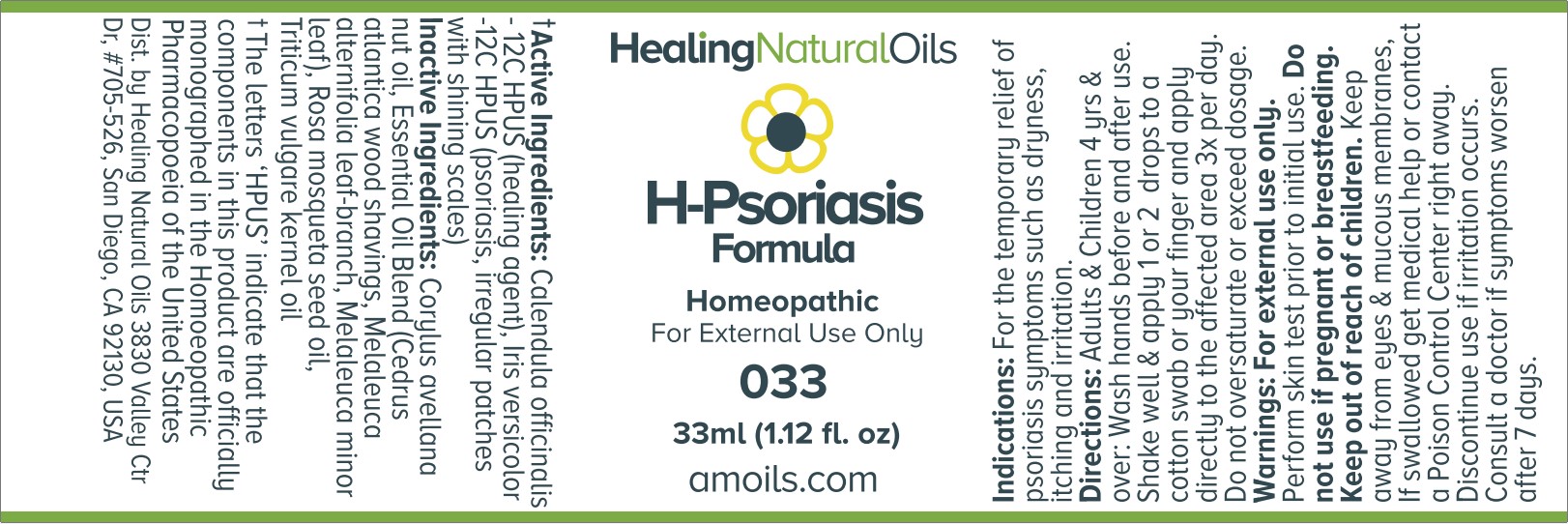 DRUG LABEL: H-Psoriasis Formula
NDC: 61077-047 | Form: OIL
Manufacturer: Healing Natural Oils LLC
Category: homeopathic | Type: HUMAN OTC DRUG LABEL
Date: 20250909

ACTIVE INGREDIENTS: CALENDULA OFFICINALIS FLOWERING TOP 12 [hp_C]/11 mL; IRIS VERSICOLOR ROOT 12 [hp_C]/11 mL
INACTIVE INGREDIENTS: CAJUPUT OIL; CEDRUS ATLANTICA BARK OIL; MELALEUCA ALTERNIFOLIA LEAF; EUROPEAN HAZELNUT OIL; WHEAT GERM OIL; ROSA MOSCHATA SEED OIL

H-Psoriasis Formula

Active Ingredients:

Calendula officinalis - 12C HPUS

Iris versicolor - 12C HPUS

Purpose

Calendula officinalis -12C HPUS (healing agent),
Iris versicolor -12CHPUS (psoriasis, irregular patches with shining scales)

The letters ‘HPUS’ indicate that the components in this product are officially monographed in the Homoeopathic Pharmacopoeia of the United States.

Indications:

For the temporary relief of psoriasis symptoms such as dryness, itching and irritation.

Directions:

Adults and Children 4 yrs and over: Wash hands before and after use.
Shake well and apply 1 or 2 drops to a cotton swab or your finger and apply directly to the affected area 3x per day.
Do not oversaturate or exceed dosage.

Warnings:

For external use only.
Perform skin test prior to initial use.

Do not use if pregnant or breastfeeding.

Keep out of reach of children.

OTHER SAFETY INFORMATION

Keep away from eyes and mucous membranes. If swallowed get medical help or contact a Poison Control
Center right away.

Discontinue use if irritation occurs.

ASK DOCTOR

Consult a doctor if symptoms worsen after 7 days.

Inactive Ingredients:

Corylus avellana nut oil, Essential Oil Blend (Cedrus atlantica wood shavings, Melaleuca alternifolia leaf-branch, Melaleuca minor leaf), Rosa mosqueta seed oil, Triticum vulgare kernel oil

DESCRIPTION

Dist. by Healing Natural Oils 3830 Valley Ctr Dr, #705-526, San Diego, CA 92130, USA

PACKAGE LABEL

Healing Natural Oils

H-Psoriasis

Formula

Homeopathic

For External Use Only

047

11ml (0.37 fl. oz)
amoils.com